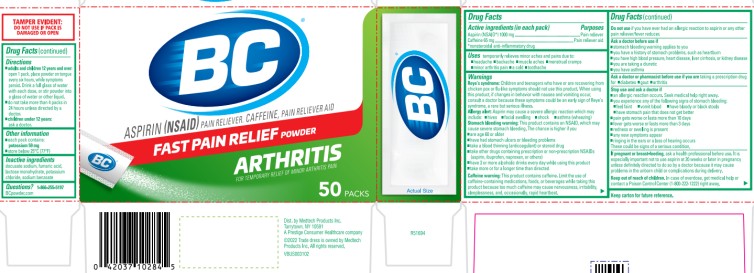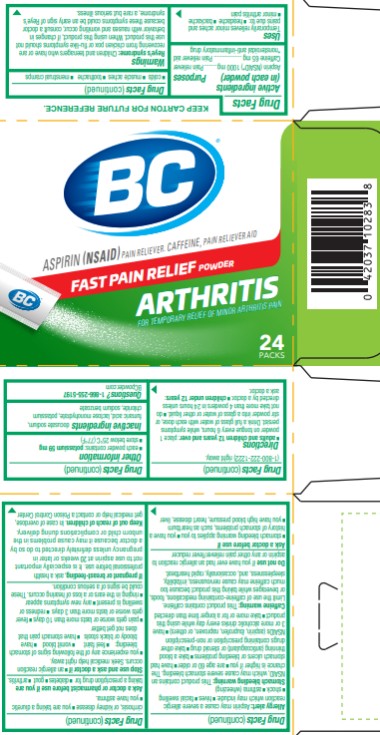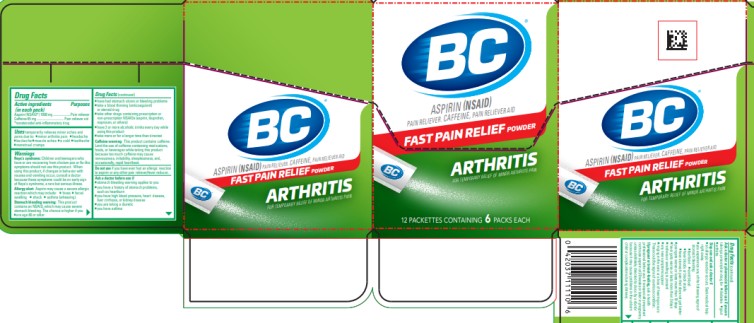 DRUG LABEL: BC Arthritis
NDC: 63029-990 | Form: POWDER
Manufacturer: Medtech Products Inc.
Category: otc | Type: HUMAN OTC DRUG LABEL
Date: 20251023

ACTIVE INGREDIENTS: ASPIRIN 1000 mg/1 1; CAFFEINE 65 mg/1 1
INACTIVE INGREDIENTS: DOCUSATE SODIUM; FUMARIC ACID; LACTOSE MONOHYDRATE; POTASSIUM CHLORIDE; SODIUM BENZOATE

BC Arthritis - 63029-990

Drug Facts

Active ingredient

(in each powder)

Aspirin (NSAID*) 1000 mg

*nonsteroidal anti-inflammatory drug

Purpose

Pain reliever/fever reducer

Active ingredient

(in each powder)

Caffeine 65 mg

Purpose

Pain reliever aid

Uses

- temporary relieves minor aches and pains due to:
  - headaches
  - backache
  - minor arthritis pain
  - colds
  - muscle aches
  - toothache
  - menstrual cramps

Warnings

Reye’s syndrome: Children and teenagers who have or are recovering from chicken pox or flu-like symptoms should not use this product. When using this product, if changes in behavior with nausea and vomiting occur, consult a doctor because these symptoms could be an early sign of Reye’s syndrome, a rare but serious illness.

Allergy alert: Aspirin may cause a severe allergic reaction which may include:

- hives
- facial swelling
- shock
- asthma (wheezing)

Stomach bleeding warning: This product contains an NSAID, which may cause severe stomach bleeding. The chance is higher if you

- are age 60 or older
- have had stomach ulcers or bleeding problems
- take a blood thinning (anticoagulant) or steroid drug
- take other drugs containing prescription or non-prescription NSAIDs (aspirin, ibuprofen, naproxen, or others)
- have 3 or more alcoholic drinks every day while using this product
- take more or for longer time than directed

Caffeine warning:

This product contains caffeine. Limit the use of caffeine-containing medications, foods, or beverages while taking this product because too much caffeine may cause nervousness, irritability, sleeplessness, and, occasionally, rapid heartbeat.

Do not use

if you have ever had an allergic reaction to aspirin or any other pain reliever/fever reducer.

Ask a doctor before use if

- stomach bleeding warnings applies to you
- you have a history of stomach problems, such as heartburn
- you have high blood pressure, heart disease, liver cirrhosis, or kidney disease
- you are taking a diuretic
- you have asthma

Ask a doctor or pharmacist before use if you are

taking a prescription drug for

- diabetes
- gout
- arthritis.

Stop use and ask a doctor if

- an allergic reaction occurs. Seek medical help right away.
- you experience any of the following signs of stomach bleeding:
  ° feel faint
  ° vomit blood
  ° have bloody or black stools
  ° have stomach pain that does not get better
- pain gets worse or lasts more than 10 days
- fever gets worse or lasts more than 3 days
- redness or swelling is present
- any new symptoms appear
- ringing in the ears or a loss of hearing occurs. These could be signs of a serious condition.

If pregnant or breast-feeding,

ask a health professional before use. It is especially important not to use aspirin at 20 weeks or later in pregnancy unless definitely directed to do so by a doctor because it may cause problems in the unborn child or complications during delivery.

Keep out of reach of children.

In case of overdose, get medical help or contact a Poison Control Center (1-800-222-1222) right away.

Directions

- adults and children 12 years of age and over: place 1 powder on tongue every 6 hours, while symptoms persist. Drink a full glass of water with each dose, or may stir powder into a glass of water or other liquid.
- do not take more than 4 powders in 24 hours unless directed by a doctor.
- children under 12 years of age: ask a doctor.

Other information

- each powder contains: potassium 59 mg
- store below 25ºC (77ºF)

Inactive ingredients

docusate sodium, fumaric acid, lactose monohydrate, potassium chloride, sodium benzoate

Questions or comments?

1-866-255-5197

BCpowder.com

PRINCIPAL DISPLAY PANEL

BC®
ASPIRIN (NSAID) – PAIN RELIEVER ● FEVER REDUCER
CAFFEINE – PAIN RELIEVER AID
FAST PAIN RELIEF
Arthritis FORMULA
FOR TEMPORARY RELIEF OF MINOR ARTHRITIS PAIN
50 POWDERS

PRINCIPAL DISPLAY PANEL

BC®
ASPIRIN (NSAID) – PAIN RELIEVER ● FEVER REDUCER
CAFFEINE – PAIN RELIEVER AID
FAST PAIN RELIEF
Arthritis FORMULA
FOR TEMPORARY RELIEF OF MINOR ARTHRITIS PAIN
24 POWDERS

PRINCIPAL DISPLAY PANEL

BC®
ASPIRIN (NSAID) – PAIN RELIEVER ● FEVER REDUCER
CAFFEINE – PAIN RELIEVER AID
FAST PAIN RELIEF
Arthritis FORMULA
FOR TEMPORARY RELIEF OF MINOR ARTHRITIS PAIN
6 POWDERS